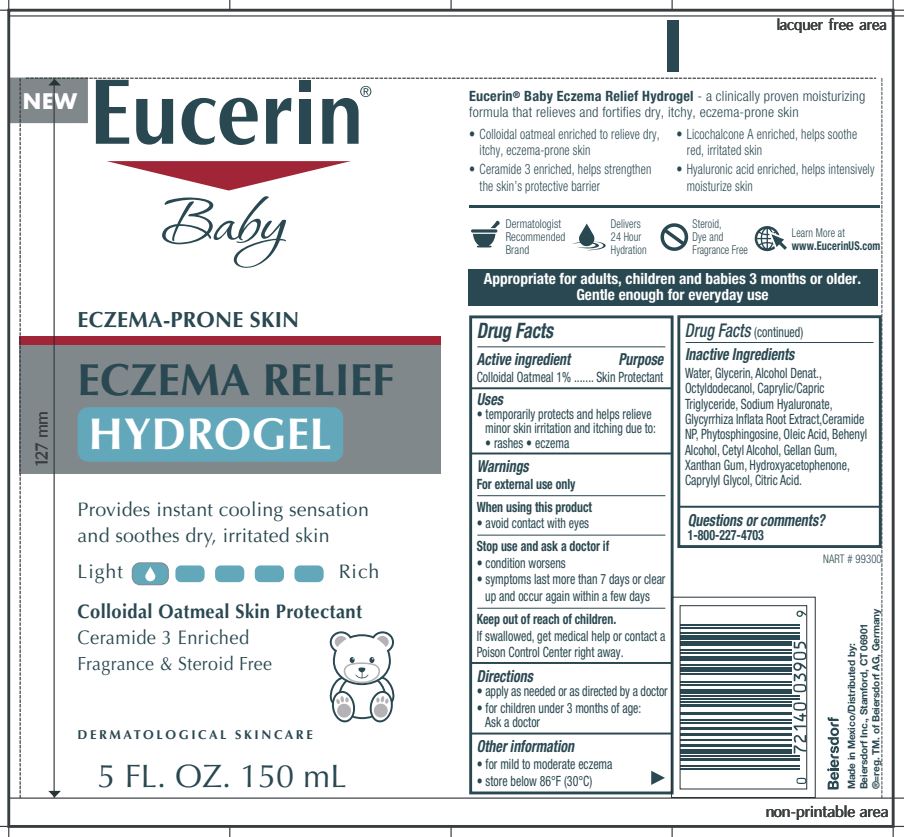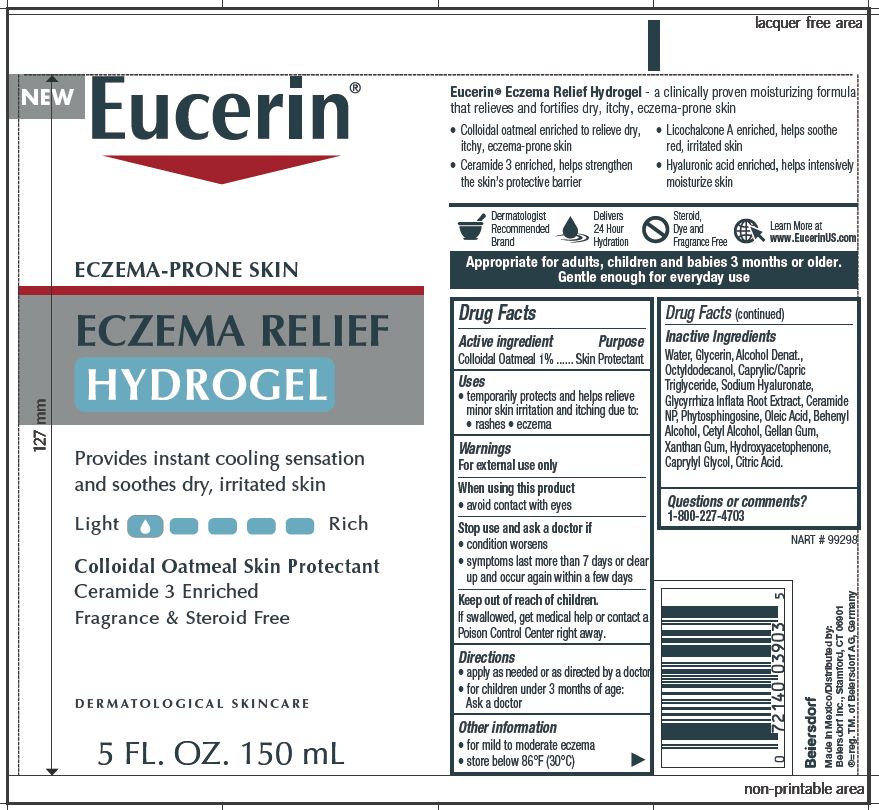 DRUG LABEL: Eucerin Eczema Relief Hydrogel
NDC: 10356-390 | Form: GEL
Manufacturer: Beiersdorf Inc
Category: otc | Type: HUMAN OTC DRUG LABEL
Date: 20251216

ACTIVE INGREDIENTS: OATMEAL 1 g/100 mL
INACTIVE INGREDIENTS: ALCOHOL; CETYL ALCOHOL; PHYTOSPHINGOSINE; CERAMIDE NP; MEDIUM-CHAIN TRIGLYCERIDES; WATER; OLEIC ACID; OCTYLDODECANOL; GLYCYRRHIZA INFLATA ROOT; GLYCERIN; GELLAN GUM (LOW ACYL); XANTHAN GUM; DOCOSANOL; HYALURONATE SODIUM; HYDROXYACETOPHENONE; CAPRYLYL GLYCOL; CITRIC ACID MONOHYDRATE

Eucerin Eczema Relief Hydrogel

Active ingredients
Colloidal Oatmeal 1%

PURPOSE

Skin protectant

Warnings
For external use only

When using this product avoid contact with eyes

Stop use and ask a doctor if
condition worsens
symptoms last more than 7 days or clear up and occur again within a few days

Keep out of reach of children. If swallowed, get medical help or
contact a Poison Control Center right away.

Uses
temporarily protects and helps relieve minor skin irritation and itching
due to rashes, eczema

Directions
apply as needed

Questions or comments?
1-800-227-4703

Inactive Ingredients
Water, Glycerin, Alcohol Denat.,
Octyldodecanol, Caprylic/Capric
Triglyceride, Sodium Hyaluronate,
Glycyrrhiza Inflata Root Extract, Ceramide
NP, Phytosphingosine, Oleic Acid, Behenyl
Alcohol, Cetyl Alcohol, Gellan Gum,
Xanthan Gum, Hydroxyacetophenone,
Caprylyl Glycol, Citric Acid.

PACKAGE LABEL

Eucerin

Eczema Relief Hydrogel

Eczema Prone Skin

Provides instant cooling sensation
and soothes dry, irritated skin

Colloidal Oatmeal Skin Protectant
Ceramide 3 Enriched
Fragrance & Steroid Free

DERMATOLOGICAL SKINCARE

Eucerin Baby

Eczema Relief Hydrogel

Eczema Prone Skin

Provides instant cooling sensation
and soothes dry, irritated skin

Colloidal Oatmeal Skin Protectant
Ceramide 3 Enriched
Fragrance & Steroid Free

DERMATOLOGICAL SKINCARE